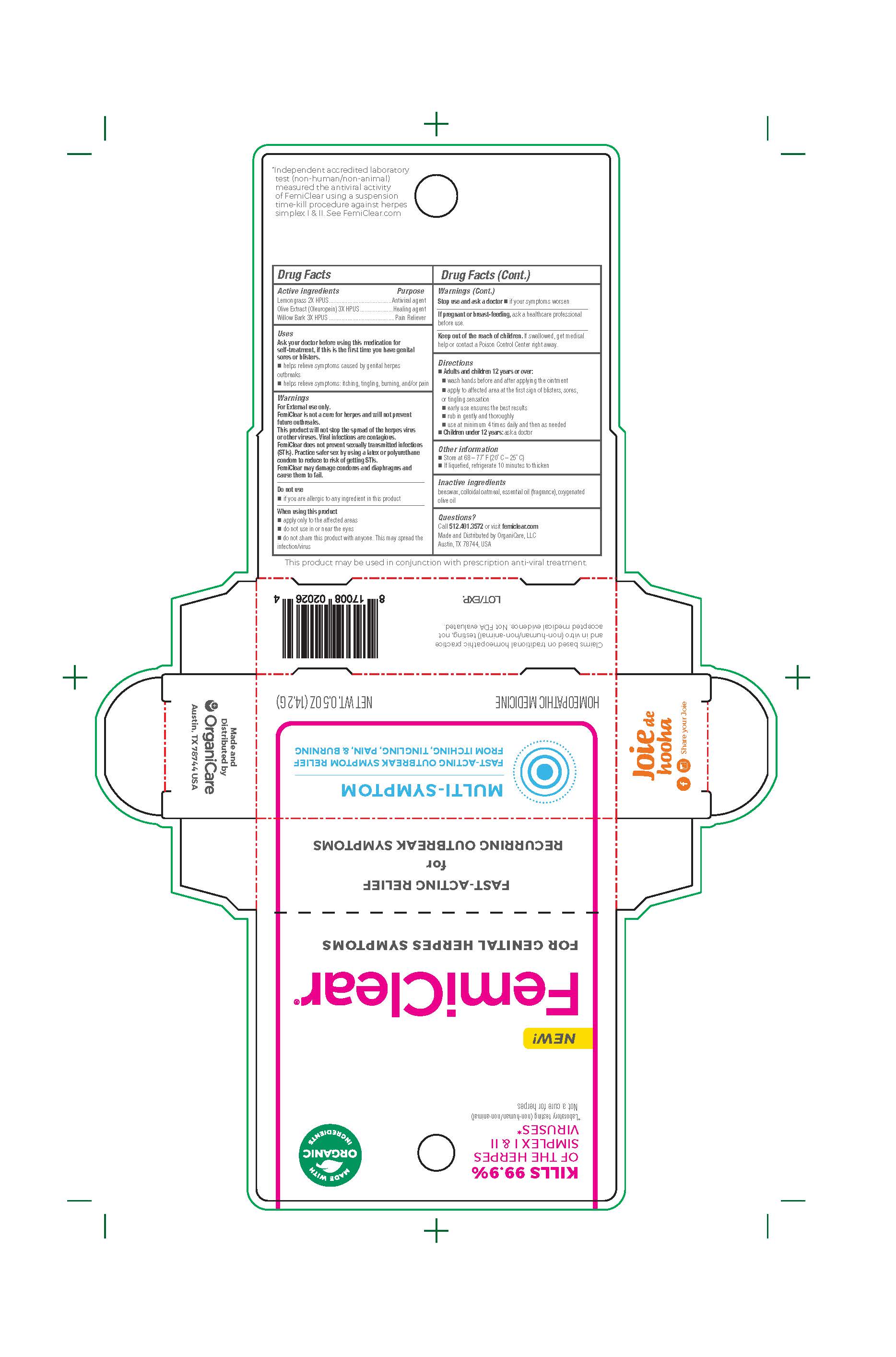 DRUG LABEL: FemiClear
NDC: 71042-020 | Form: OINTMENT
Manufacturer: Organicare Nature's Science, LLC
Category: homeopathic | Type: HUMAN OTC DRUG LABEL
Date: 20251020

ACTIVE INGREDIENTS: WILLOW BARK 3 [hp_X]/100 g; OLEA EUROPAEA FRUIT VOLATILE OIL 3 [hp_X]/100 g; EAST INDIAN LEMONGRASS OIL 2 [hp_X]/100 g
INACTIVE INGREDIENTS: OATMEAL; YELLOW WAX; OLIVE OIL

FemiClear for Genital Herpes Symptoms

Active Ingredients

Lemongrass 2X HPUS

Olive Extract (Oleuropein) 3X HPUS

Willow Bark 3X HPUS

Purpose

Antiviral agent

Healing agent

Pain Reliever

Uses

Ask your doctor before using this medication for self-treatment, if this is the first time you have genital sores or blisters

helps relieve symptoms caused by genital herpes outbreaks

helps relieve symptoms: Itching, tingling, burning, and/or pain

Warnings

For external use only.

FemiClear is not a cure for herpes and will not prevent future outbreaks.

This product will not stop the spread of herpes viruses or other viruses. Viral infections are contagious.

FemiClear does not prevent sexually transmitted infections (STIs). Practice safer sex by using latex or polyurethane condom to reduce risk of getting STIs.

FemiClear may damage condoms and diaphragms and cause ethem to fail

Do not use

if you are allergic to any ingredient in this product

When using this product

apply only to affected areas

Do not use in or near the eyes

do not share this product with anyone. This may spread the infection/virus

Stop use and ask a doctor

if your symptoms worsen

If pregnant or breast-feeding

ask a healthcare professional before use.

Keep out of the reach of children

If swallowed, get medical help or contact Poison Control Center right away

Directions

Adults and children 12 years of age and older:

- wash hands before and after applying the ointment
- apply to affected area t teh first sign of blister, sores, or tingling sensation
- early use ensures the best results
- rub in gently and thoroughly
- use at minimum 4 times daily and then as needed

Children under 12 years: ask a doctor

Inactve ingredients

Beeswax, colloidal oatmeal, essential oil (fragrance), oxygenated olive oil

Claims based on traditional homeopathic practice, not accepted medical evidence. Not FDA evaluated.

Made and Distributed by

Organicare

Austin, TX 78744, USA

PACKAGE LABEL

MADE WITH ORGANICINGREDIENTS

FemiClear®

FOR GENITAL HERPES SYMPTOMS

FAST-ACTING RELIEF

FOR RECURRING OUTBREAK SYMPTOMS

MULTI-SYMPTOM

FAST-ACTING OUTBREAK SYMPTOM RELIEF FROM ITCHING, TINGLING, PAIN, & BURNING

HOMEPATHIC MEDICINE

NET WT. 0.5OZ(14.2G)